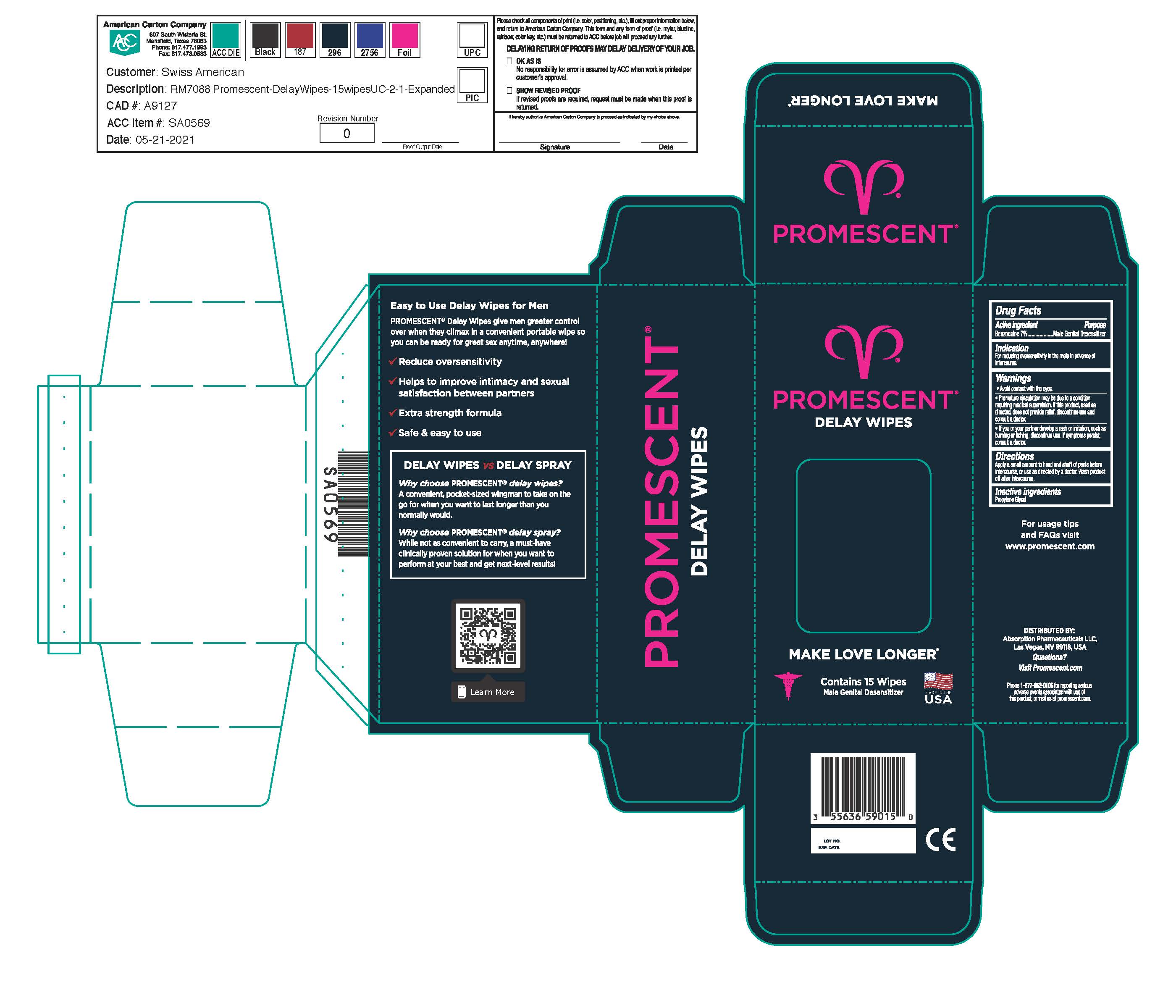 DRUG LABEL: Promescent Delay Wipes
NDC: 55636-000 | Form: DRESSING
Manufacturer: Absorption
Category: otc | Type: HUMAN OTC DRUG LABEL
Date: 20240220

ACTIVE INGREDIENTS: BENZOCAINE 70 g/1000 g
INACTIVE INGREDIENTS: PROPYLENE GLYCOL

Promescent Delay Wipes

Warnings

Avoid contact with the eyes.

Premature ejaculation may be due to a condition requiring medical supervision. If this product, used as directed, does not provide relief, discontinue use and consult a doctor.

If you or your partner develop a rash or irritation, such as burning or itching, discontinue use. If symptoms persist, consult a doctor.

Directions

Apply a small amount to head and shaft of penis before intercourse, or use as directed by a doctor. Wash product off after intercourse.

Indications

For reducing oversensitivity in the male in advance of intercourse.

Indications

For reducing oversensitivity in the male in advance of intercourse.

Active Ingredients

Benzocaine 7% Male Genital Desensitizer

Inactive Ingredient

Propylene glycol

Questions?

Visit Promescent.com

Keep out of reach of children

Other Information

Distributed by: Absorption Pharmaceuticals LLC, Las Vegas, NV 89118, USA. Phone 1-877-852-0106 for reporting serious adverse events associated with use of this product, or visit promescent.com